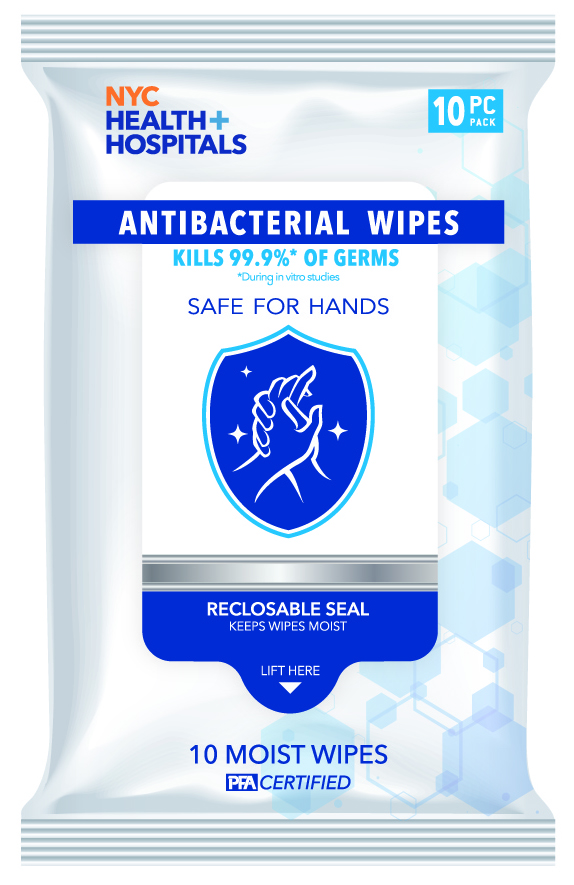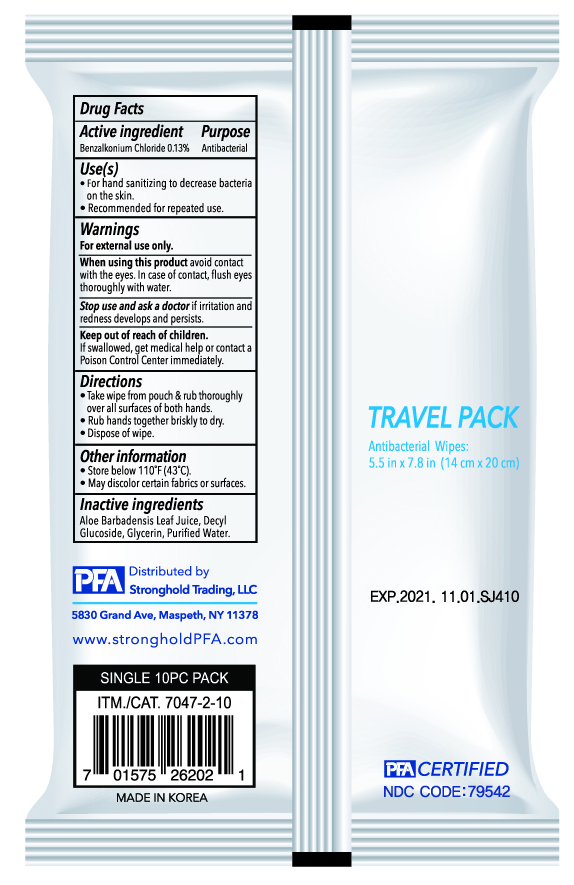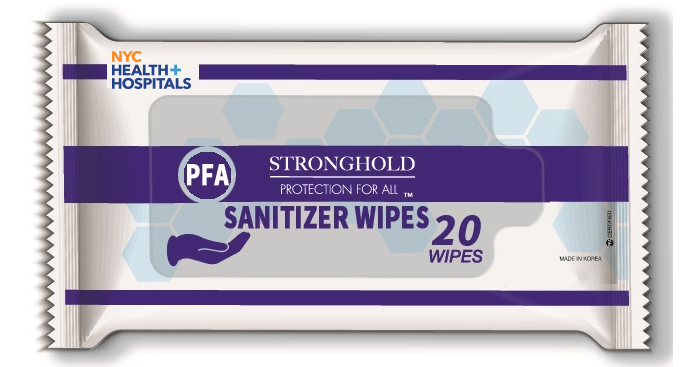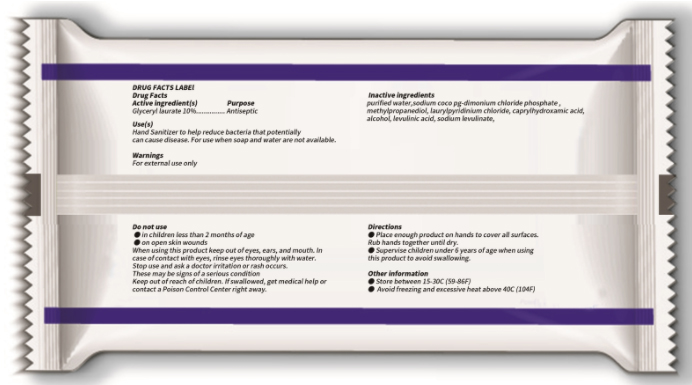 DRUG LABEL: Mi Deurium Antibacterial Wet Wipes
NDC: 79542-201 | Form: LIQUID
Manufacturer: SEOJEON CO., LTD
Category: otc | Type: HUMAN OTC DRUG LABEL
Date: 20231228

ACTIVE INGREDIENTS: GLYCERYL LAURATE 10 g/100 g
INACTIVE INGREDIENTS: CAPRYLHYDROXAMIC ACID; LEVULINIC ACID; SODIUM LEVULINATE; LAURYLPYRIDINIUM CHLORIDE; WATER; ALCOHOL; METHYLPROPANEDIOL

Active ingredient

Glyceryl laurate 10%

Purpose

Antiseptic

Use

Hand Sanitizer to help reduce bacteria that potentially can cause disease. For use when soap and water are not available.

Warnings

For external use only

Do not use

● in children less than 2 months of age

● on open skin wounds

When using this product

keep out of eyes, ears, and mouth. In case of contact with eyes, rinse eyes thoroughly with water.

Stop use and ask a doctor

irritation or rash occurs. These may be signs of a serious condition.

Keep out of reach of children.

If swallowed, get medical help or contact a Poison Control Center right away.

Directions

● Place enough product on hands to cover all surfaces. Rub hands together until dry.

● Supervise children under 6 years of age when using this product to avoid swallowing.

Other information

● Store between 15-30C (59-86F)

● Avoid freezing and excessive heat above 40C (104F)

Inactive ingredients

purified water, sodium coco pg-dimonium chloride phosphate, methylpropanediol, laurylpyridinium chloride, caprylhydroxamic acid, alcohol, levulinic acid, sodium levulinate